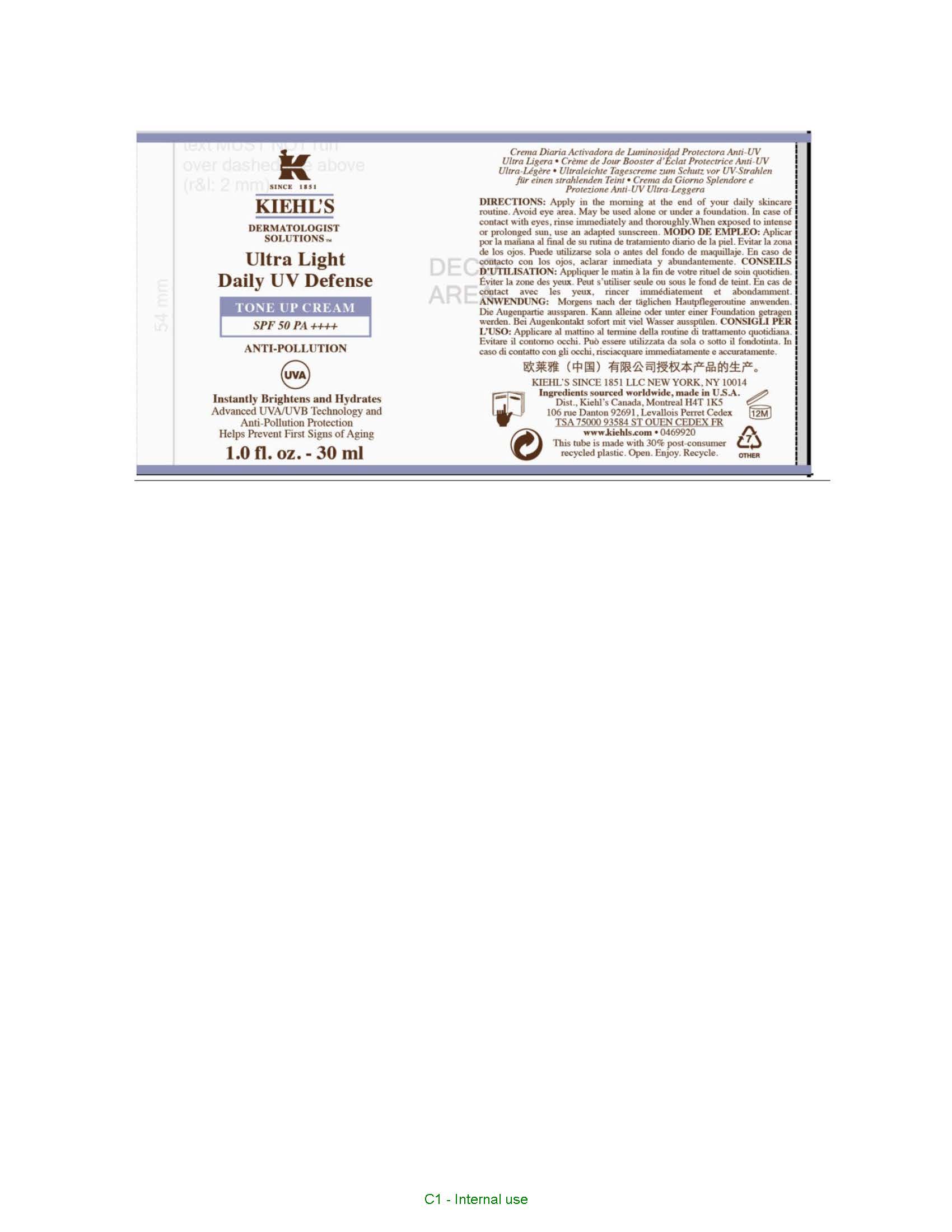 DRUG LABEL: KIEHLS ULTRA LIGHT DAILY UV DEFENSE TONE UP SPF 50 ANTI POLLUTION INSTANTLY BRIGHTENS AND HYDRATES
NDC: 49967-762 | Form: CREAM
Manufacturer: L'Oreal USA Products Inc
Category: otc | Type: HUMAN OTC DRUG LABEL
Date: 20260107

ACTIVE INGREDIENTS: ECAMSULE 39.6 mg/1 mL; OCTINOXATE 67.4 mg/1 mL; TITANIUM DIOXIDE 32.8 mg/1 mL
INACTIVE INGREDIENTS: TROLAMINE; ADENOSINE; SORBITAN MONOOLEATE; ISOHEXADECANE; WATER; POLYSORBATE 80; DIMETHICONE; SCUTELLARIA BAICALENSIS ROOT; GLYCERYL MONOSTEARATE; PEG-100 STEARATE; POLYSORBATE 60; SORBITAN ISOSTEARATE; CITRIC ACID MONOHYDRATE; DISODIUM STEAROYL GLUTAMATE; ALCOHOL; SODIUM COCOYL SARCOSINATE; SODIUM CHLORIDE; ISOCETYL STEARATE; BUTYLATED HYDROXYTOLUENE; EDETATE DISODIUM; TOCOPHEROL; DIETHYLAMINO HYDROXYBENZOYL HEXYL BENZOATE; GLYCERIN; PROPYLENE GLYCOL; CAPRYLYL GLYCOL; PHENOXYETHANOL; XANTHAN GUM; ETHYLHEXYL HYDROXYSTEARATE; BISMUTH OXYCHLORIDE; PELARGONIUM GRAVEOLENS FLOWER OIL; ORANGE OIL; POTASSIUM CETYL PHOSPHATE; CETYL ALCOHOL; LITCHI FRUIT; BUTYLENE GLYCOL; POWDERED CELLULOSE; MYRISTIC ACID; PALMITIC ACID; STEARIC ACID; DROMETRIZOLE TRISILOXANE; ALUMINUM HYDROXIDE

Drug Facts

Directions

Apply in the morning at the end of your daily skincare routine. Avoid eye area. May be used alone or under a foundation. In case of contact with eyes, rinse immediately and thoroughly. When exposed to intense or prolonged sun, use an adapted sunscreen.